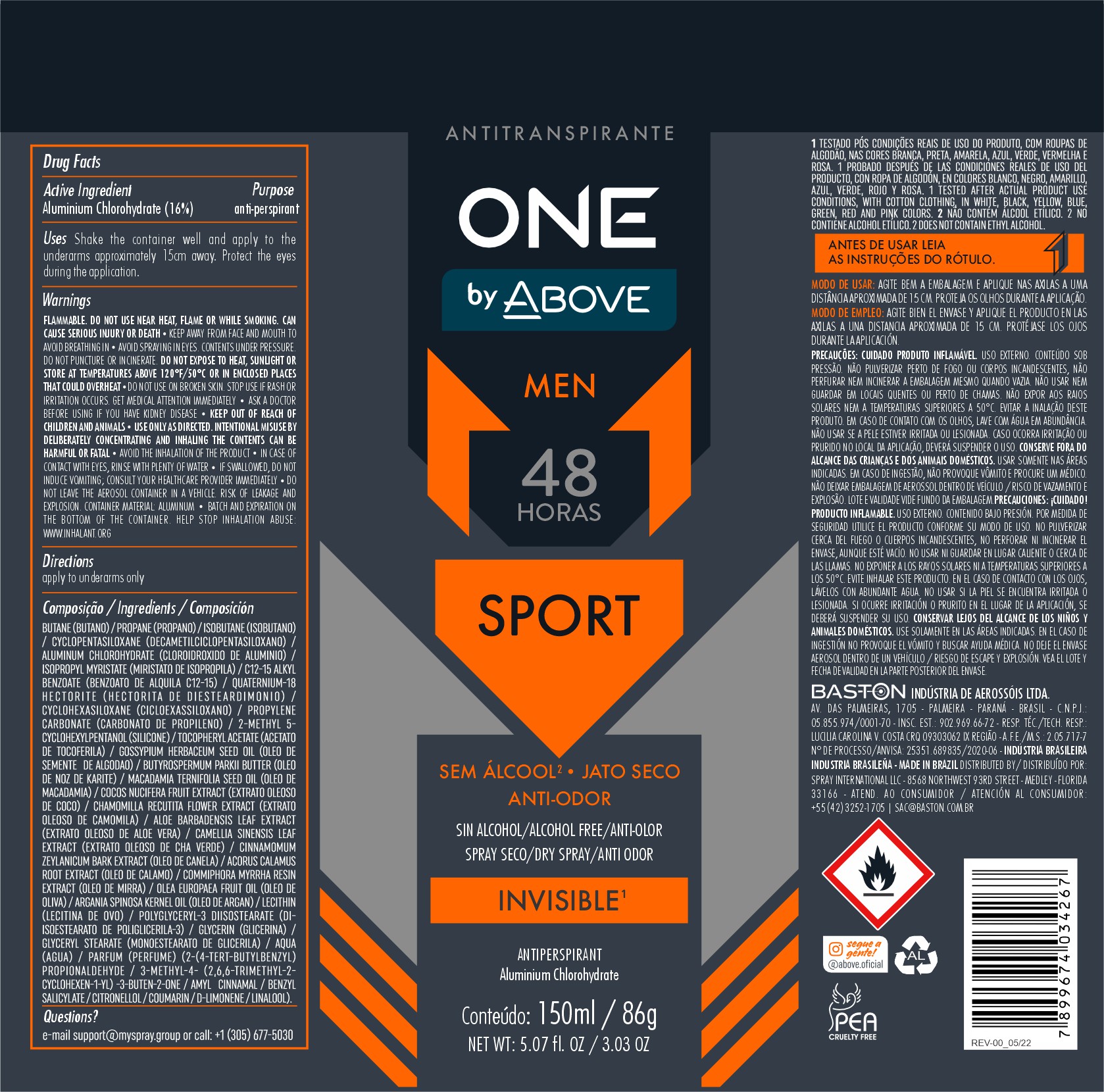 DRUG LABEL: ANTIPERSPIRANT ABOVE ONE BY SPORT MEN
NDC: 73306-1140 | Form: AEROSOL, SPRAY
Manufacturer: BASTON INDUSTRIA DE AEROSSOIS LTDA
Category: otc | Type: HUMAN OTC DRUG LABEL
Date: 20241226

ACTIVE INGREDIENTS: ALUMINUM CHLOROHYDRATE 100 g/100 g
INACTIVE INGREDIENTS: ISOPROPYL MYRISTATE; ISOBUTANE

ANTIPERSPIRANT ABOVE ONE BY SPORT MEN

ANTIPERSPIRANT

QUESTIONS

SUPPORT@MYSPRAY.GROUP OR CALL (305) 677-5030

WARNINGS AND PRECAUTIONS

Warnings: Flammable. Do not use near heat, flame or while smoking, can cause serious injury or death. Keep away from face and mouth avoid breathing in avoid spraying in eyes. Contents under pressure. Do not puncture or incinerate. Do not expose to heat, sunlight or store at temperatures above 120ºF/50ºC or in enclosed places that could overheat. do not use on broken skin. stop ude if rash or irritation occurs. get medical attention immediately ask a doctor before using if you have kidney disease. keep out of reach ok children and animals. use only as directed. intentional misuse by deliberately concentrating and inhaling the contents can be harmeful or fatal. avoid the inhalation of the product . in case of contact with eyes, rinse with plenty of water. if swallowed, do not leave the aerosol container in a vehicle. risk of leakage and explosion. container material: aluminum. batch help stop ilhalation abuse: www.inhalant.org

apply to underarms only

KEEP OUT OF CHILDREN

Do not use near heat, flame or while smoking, can cause serious injury or death. Keep away from face and mouth avoid breathing in avoid spraying in eyes. Contents under pressure. Do not puncture or incinerate. Do not expose to heat, sunlight or store at temperatures above 120ºF/50ºC or in enclosed places that could overheat. do not use on broken skin. stop ude if rash or irritation occurs. get medical attention immediately ask a doctor before using if you have kidney disease. keep out of reach ok children and animals. use only as directed. intentional misuse by deliberately concentrating and inhaling the contents can be harmeful or fatal. avoid the inhalation of the product . in case of contact with eyes, rinse with plenty of water. if swallowed, do not leave the aerosol container in a vehicle. risk of leakage and explosion. container material: aluminum. batch help stop ilhalation abuse: www.inhalant.org

INACTIVE INGREDIENT

BUTANE
PROPANE
ISOBUTANE
CYCLOPENTASILOXANE
ALUMINUM CHLOROHYDRATE
ISOPROPYL MYRISTATE
PARFUM
C12-15 ALKYL BENZOATE
QUATERNIUM-18 HECTORITE
CYCLOHEXASILOXANE
PROPYLENE CARBONATE
2-METHYL 5-CYCLOHEXYLPENTANOL
TOCOPHERYL ACETATE
GOSSYPIUM HERBACEUM SEED OIL
BUTYROSPERMUM PARKII BUTTER
MACADAMIA TERNIFOLIA SEED OIL
COCOS NUCIFERA FRUIT EXTRACT
CHAMOMILLA RECUTITA FLOWER EXTRACT
ALOE BARBADENSIS LEAF EXTRACT
CAMELLIA SINENSIS LEAF EXTRACT
CINNAMOMUM ZEYLANICUM BARK EXTRACT
ACORUS CALAMUS ROOT EXTRACT
COMMIPHORA MYRRHA RESIN EXTRACT
OLEA EUROPAEA FRUIT OIL
ARGANIA SPINOSA KERNEL OIL
LECITHIN
POLYGLYCERYL-3 DIISOSTEARATE
GLYCERIN
GLYCERYL STEARATE
AQUA